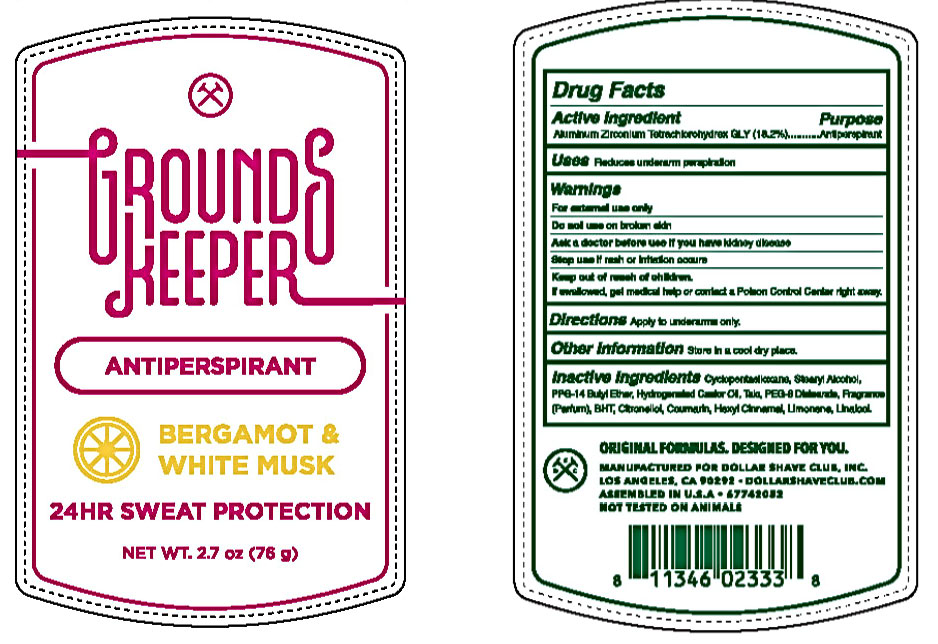 DRUG LABEL: Dollar Shave Club Grounds Keeper
NDC: 69522-2615 | Form: STICK
Manufacturer: Dollar Shave Club, Inc.
Category: otc | Type: HUMAN OTC DRUG LABEL
Date: 20241107

ACTIVE INGREDIENTS: ALUMINUM ZIRCONIUM TETRACHLOROHYDREX GLY 18.2 g/100 g
INACTIVE INGREDIENTS: COUMARIN; .ALPHA.-HEXYLCINNAMALDEHYDE; HYDROGENATED CASTOR OIL; PEG-8 DISTEARATE; TALC; CYCLOMETHICONE 5; BUTYLATED HYDROXYTOLUENE; PPG-14 BUTYL ETHER; STEARYL ALCOHOL; .BETA.-CITRONELLOL, (R)-; LIMONENE, (+)-; LINALOOL, (+/-)-

Dollar Shave Club Grounds Keeper 24HR Protection Bergamot and White Musk Antiperspirant

DOLLAR SHAVE CLUB GROUNDS KEEPER 24HR PROTECTION BERGAMOT AND WHITE MUSK ANTIPERSPIRANT - aluminum zirconium tetrachlorohydrex gly stick

Dollar Shave Club Grounds Keeper 24HR Protection Bergamot and White Musk Antiperspirant

Drug Facts

Active ingredient

Aluminum Zirconium Tetrachlorohydrex GLY (18.2 %)

Purpose

antiperspirant

Uses

• reduces underarm perspiration

Warnings

• For externaluse only.
• Do not use on broken skin .
• Ask a doctor before use if you have kidney disease.
• Stop use if rash or irritation occurs.

• Keep out of reach of children.

If swallowed, get medical help or contact a Poison Control Center right away.

Directions

apply to underarms only

Inactive ingredients

Cyclopentasiloxane, Stearyl Alcohol, PPG-14 Butyl Ether, Hydrogenated Castor Oil, Talc, PEG-8 Distearate, Fragrance (Parfum), BHT, Citronellol, Coumarin, Hexyl Cinnamal, Limonene, Linalool.

Other Information

Store in a cool dry place